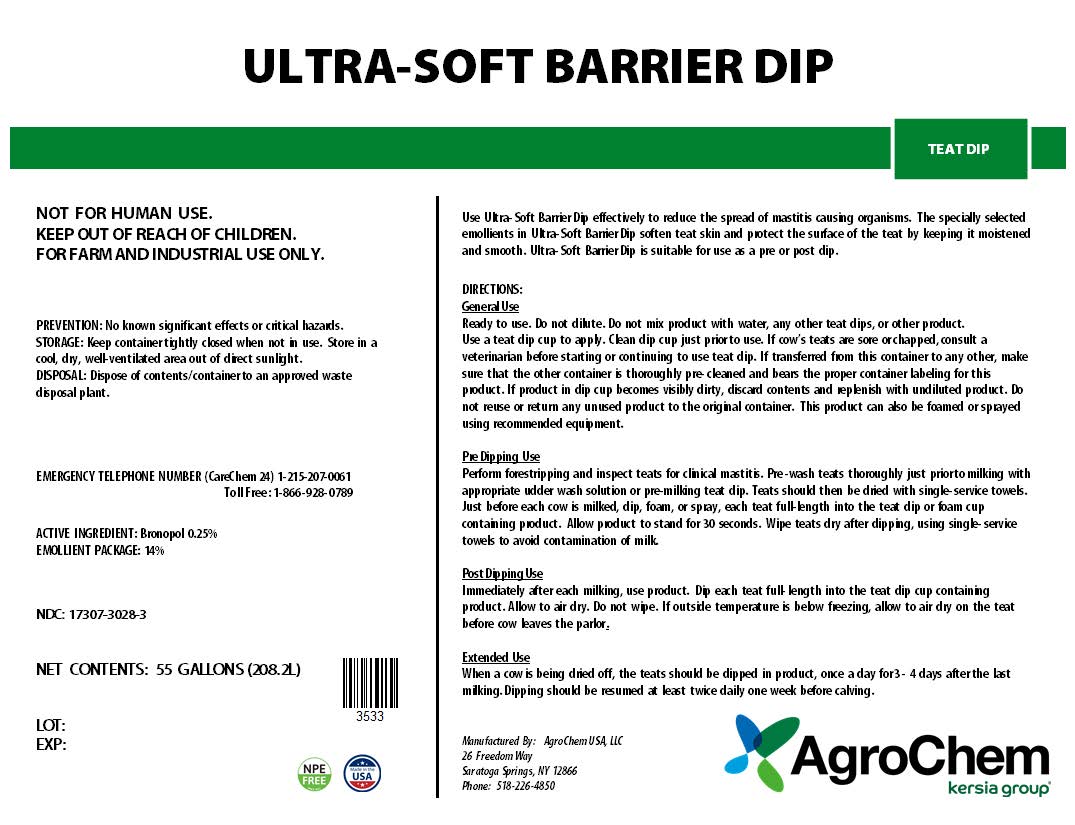 DRUG LABEL: ULTRA-SOFT BARRIER DIP
NDC: 17307-3028 | Form: SOLUTION
Manufacturer: AgroChem USA, LLC.
Category: animal | Type: OTC ANIMAL DRUG LABEL
Date: 20241101

ACTIVE INGREDIENTS: BRONOPOL 0.0025 kg/1 kg

ULTRA-SOFT BARRIER DIP

ULTRA-SOFT BARRIER

TEAT DIP

KEEP OUT OF REACH OF CHILDREN.

WARNINGS AND PRECAUTIONS

NOT FOR HUMAN USE.

FOR FARM AND INDUSTRIAL USE ONLY.

PREVENTION: No known significant effects or critical hazards.

STORAGE AND HANDLING

STORAGE: Keep container tightly closed when not in use. Store in a cool, dry, well-ventilated area out of direct sunlight.

DISPOSAL: Dispose of contents/ container to an approved waste disposal plant.

EMERGENCY TELEPHONE NUMBER (CareChem 24) 1-215-207-0061

Toll Free: 1-866-928-0789

Active Ingredients: Bronopol – 0.25%

INACTIVE INGREDIENT

Emollients Package: 14%

NDC: 17307-3028-3

NET CONTENTS: 55 GALLONS (208.2L)

LOT:

EXP:

Use Ultra- Soft Barrier Dip effectively to reduce the spread of mastitis causing organisms. The specially selected emollients in Ultra- Soft Barrier Dip soften teat skin and protect the surface of the teat by keeping it moistened and smooth. Ultra- Soft Barrier Dip is suitable for use as a pre or post dip.

DIRECTIONS:

General Use

Ready to use. Do not dilute. Do not mix product with water, any other teat dips, or other product.

Use a teat dip cup to apply. Clean dip cup just prior to use. If cow’s teats are sore or chapped, consult a veterinarian before starting or continuing to use teat dip. If transferred from this container to any other, make sure that the other container is thoroughly pre- cleaned and bears the proper container labeling for this product. If product in dip cup becomes visibly dirty, discard contents and replenish with undiluted product. Do not reuse or return any unused product to the original container. This product can also be foamed or sprayed using recommended equipment.

Pre Dipping Use

Perform forestripping and inspect teats for clinical mastitis. Pre -wash teats thoroughly just prior to milking with appropriate udder wash solution or pre-milking teat dip. Teats should then be dried with single- service towels. Just before each cow is milked, dip, foam, or spray, each teat full-length into the teat dip or foam cup containing product. Allow product to stand for 30 seconds. Wipe teats dry after dipping, using single- service towels to avoid contamination of milk.

Post Dipping Use

Immediately after each milking, use product. Dip each teat full- length into the teat dip cup containing product. Allow to air dry. Do not wipe. If outside temperature is below freezing, allow to air dry on the teat before cow leaves the parlor.

Extended Use

When a cow is being dried off, the teats should be dipped in product, once a day for 3 - 4 days after the last milking. Dipping should be resumed at least twice daily one week before calving.

Manufactured By: AgroChem USA, LLC 26 Freedom Way • Saratoga Springs, NY 12866 • (518)226-4850